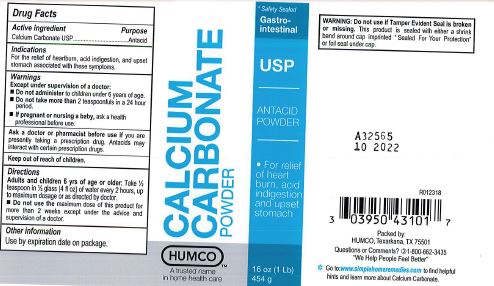 DRUG LABEL: Calcium Carbonate
NDC: 0395-0431 | Form: POWDER
Manufacturer: Humco Holding Group, Inc.
Category: otc | Type: HUMAN OTC DRUG LABEL
Date: 20231215

ACTIVE INGREDIENTS: CALCIUM CARBONATE 1 g/1 g
INACTIVE INGREDIENTS: WATER

Humco Calcium Carbonate, USP

Drug Facts

Active Ingredient

Calcium Carbonate

Purpose

Antacid

Use

For relief of heartburn, acid ingestion, and upset stomach associated with these symptoms.

Warnings

Except under the supervision of a doctor:

- do not administer to children under 6 years of age.
- do not take more than 3 teaspoonfuls in a 24 hour period.

- do not use the maximum dosge of this product for more than 2 weeks except under the advice and supervision of a doctor or other health professional.

Ask a doctor before use

if you are preganant or nursing a baby.

Keep out of reach of children.

In case of accidental overdose, seek professional assistance or contact a Poison Control immediately.

Directions

Adults and children 6 yrs. of age and older: Take 1/2 level tsp. in 1/2 glass (4 fl oz) of water every 2 hrs. up to maximum dosage or as directed by a doctor.

Inactive Ingredients

None